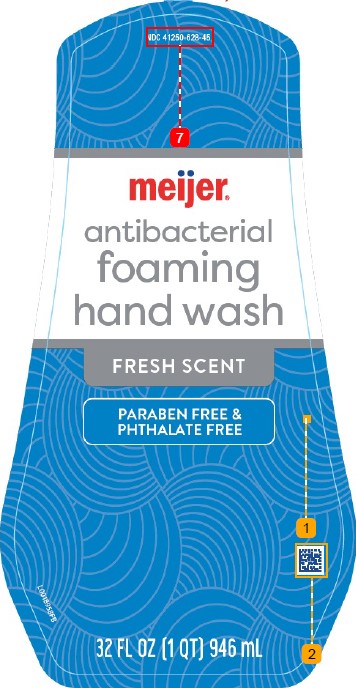 DRUG LABEL: Hand Wash
NDC: 41250-628 | Form: LIQUID
Manufacturer: Meijer, Inc.
Category: otc | Type: HUMAN OTC DRUG LABEL
Date: 20260219

ACTIVE INGREDIENTS: BENZALKONIUM CHLORIDE 1.3 mg/1 mL
INACTIVE INGREDIENTS: WATER; COCAMIDOPROPYL BETAINE; LAURAMIDOPROPYLAMINE OXIDE; LAURAMINE OXIDE; MYRISTAMIDOPROPYLAMINE OXIDE; GLYCERIN; CITRIC ACID MONOHYDRATE; EDETATE SODIUM; SULISOBENZONE; SODIUM BENZOATE; FD&C BLUE NO. 1; D&C RED NO. 33

Meijer 628.002/628AF
Antibacterial Foaming Hand Wash

Active ingredient

Benzalkonium chloride 0.13%

Purpose

Antibacterial

Use

for handwashing to decrease bacteria on the skin

Warnings

For external use only: hands only

When using this product

- avoid contact with eyes. If contact occurs, rinse eyes thoroughly with water.

Stop use and ask a doctor if

- irritation and redness develop
- condition persists for more than 72 hours

Keep out of reach of children.

if swallowed, get medical help or contact a Poison Control Center right away.

Directions

- wet hands
- apply palmful to hands
- scrub thoroughly
- rinse thoroughly

Inactive ingredients

water, cocamidopropyl betaine, lauramidopropylamine oxide, lauramine oxide, myristamidopropylamine oxide, glycerin, fragrance, citric acid, tetrasodium EDTA, benzophenone-4, sodium benzoate, blue 1, red 33

Questions?

Call 1-888-593-0593

Adverse reactions

DISTRIBUTED BY MEIJER DISTRIBUTION, INC.

GRAND RAPIDS, MI 49544

www.meijer.com

OUR QUALITY GUARANTEE

The Meijer Family

www.meijer.com/satisfaction

Empty Before Recycling

PLASTIC BOTTLE

how2recycle.info

principal display panel

NDC 41250-628-45

meijer ®

antibacterial

foaming

hand wash

FRESH SCENT

PARABEN FREE &

PHTHALATE FREE

32 FL OZ (1 QT) 946 mL